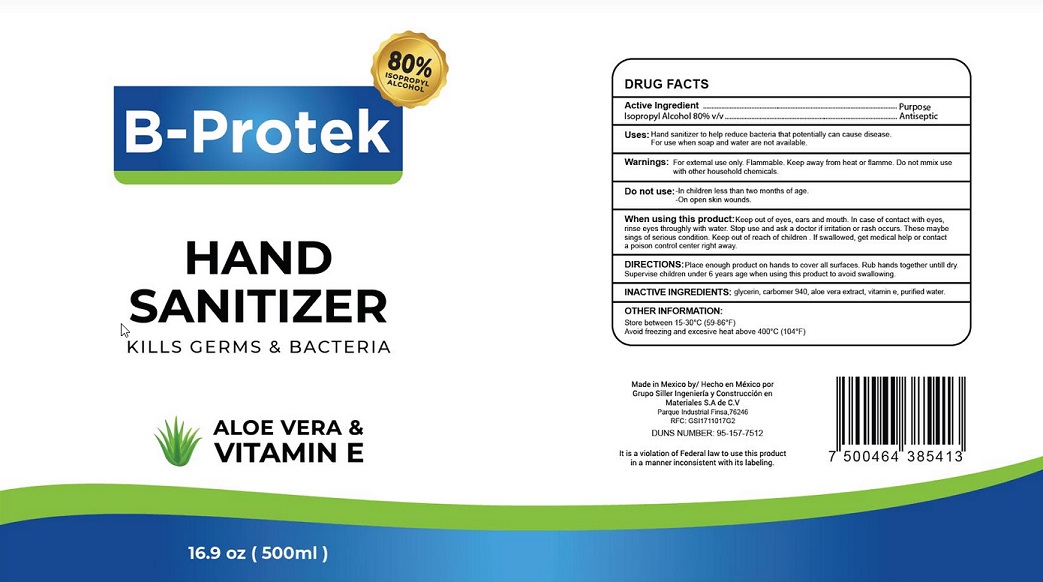 DRUG LABEL: B-Protek
NDC: 80308-002 | Form: GEL
Manufacturer: Grupo Siller Ingeniería Construcción y Materiales, S.A. de C.V
Category: otc | Type: HUMAN OTC DRUG LABEL
Date: 20200924

ACTIVE INGREDIENTS: ISOPROPYL ALCOHOL 80 mL/100 mL
INACTIVE INGREDIENTS: GLYCERIN; CARBOMER HOMOPOLYMER TYPE C (ALLYL PENTAERYTHRITOL CROSSLINKED); ALOE VERA LEAF; WATER; .ALPHA.-TOCOPHEROL; TROLAMINE

Active Ingredient

Isopropyl Alcohol 80% v/v.

Purpose

Antiseptic

Use

Hand Sanitizer to help reduce bacteria that potentially can cause disease. For use when soap and water are not available.

Warnings

For external use only. Flammable. Keep away from heat or flame.

Do not mix use with other household chemicals.

Do not use

- in children less than 2 months of age
- on open skin wounds

When using this product keep out of eyes, ears, and mouth. In case of contact with eyes, rinse eyes thoroughly with water.
Stop use and ask a doctor if irritation or rash occurs. These may be signs of a serious condition.

Keep out of reach of children. If swallowed, get medical help or contact a Poison Control Center right away.

Directions

- Place enough product on hands to cover all surfaces. Rub hands together until dry.
- Supervise children under 6 years of age when using this product to avoid swallowing.

Other information

- Store between 15-30C (59-86F)
- Avoid freezing and excessive heat above 40C (104F)

Inactive ingredients

Glycerin, carbomer 940, aloe vera extract, vitamin E, purified water.